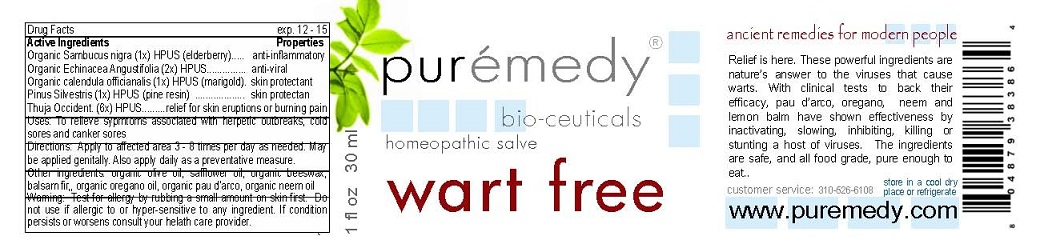 DRUG LABEL: WART FREE
NDC: 52810-701 | Form: SALVE
Manufacturer: PUREMEDY
Category: homeopathic | Type: HUMAN OTC DRUG LABEL
Date: 20211219

ACTIVE INGREDIENTS: THUJA OCCIDENTALIS WHOLE 6 [hp_X]/100 mL; SAMBUCUS NIGRA FLOWER 1 [hp_X]/100 mL; CALENDULA OFFICINALIS FLOWER 1 [hp_X]/100 mL; ECHINACEA ANGUSTIFOLIA 2 [hp_X]/100 mL; PINE NEEDLE OIL (PINUS SYLVESTRIS) 1 [hp_X]/100 mL
INACTIVE INGREDIENTS: ABIES BALSAMEA LEAF OIL; OREGANO LEAF OIL; TABEBUIA IMPETIGINOSA WHOLE; AZADIRACHTA INDICA SEED OIL; OLIVE OIL; SAFFLOWER OIL; YELLOW WAX

WART FREE (52810-701)

ACTIVE INGREDIENTS

ORGANIC SAMBUCUS NIGRA (1X) HPUS (ELDERBERRY)

ORGANIC ECHINACEA ANGUSTIFOLIA (2X) HPUS

ORGANIC CALENDULA OFFICINALIS (1X) HPUS (MARIGOLD)

PINUS SYLVESTRIS (1X) HPUS (PINE RESIN)

THUJA OCCIDENT. (6X) HPUS

PURPOSE

PROPERTIES

ANTI-INFLAMMATORY

ANTI-VIRAL

SKIN PROTECTANT

SKIN PROTECTANT

RELIEF FOR SKIN ERUPTIONS OR BURNING PAIN

INDICATIONS AND USAGE

USES: TO RELIEVE SYMPTOMS ASSOCIATED WITH HERPETIC OUTBREAKS, COLD SORES AND CANKER SORES.

DOSAGE AND ADMINISTRATION

DIRECTIONS: APPLY TO AFFECTED AREA 3-8 TIMES PER DAY OR AS NEEDED. MAY BE APPLIED GENITALLY. ALSO APPLY DAILY AS A PREVENTATIV MEASURE.

INACTIVE INGREDIENT

OTHER INGREDIENTS: ORGANIC OLIVE OIL, SAFFLOWER OIL, ORGANIC BEESWAX, BALSAM FIR, ORGANIC OREGANO OIL, ORGANIC PAU D'ARCO, ORGANIC NEEM OIL

WARNINGS

WARNING: TEST FOR ALLERGY BY RUBBING A SMALL AMOUNT ON SKIN FIRST. DO NOT USE IF ALLERGIC TO OR HYPER-SENSITIVE TO ANY INGREDIENT IN THIS SALVE. IF CONDITION PERSISTS OR WORSENS CONSULT YOUR HEALTH CARE PROVIDER. (* = CERTIFIED ORGANIC INGREDIENTS)

KEEP OUT OF REACH OF CHILDREN.

QUESTIONS

CUSTOMER SERVICE: 310-526-6108